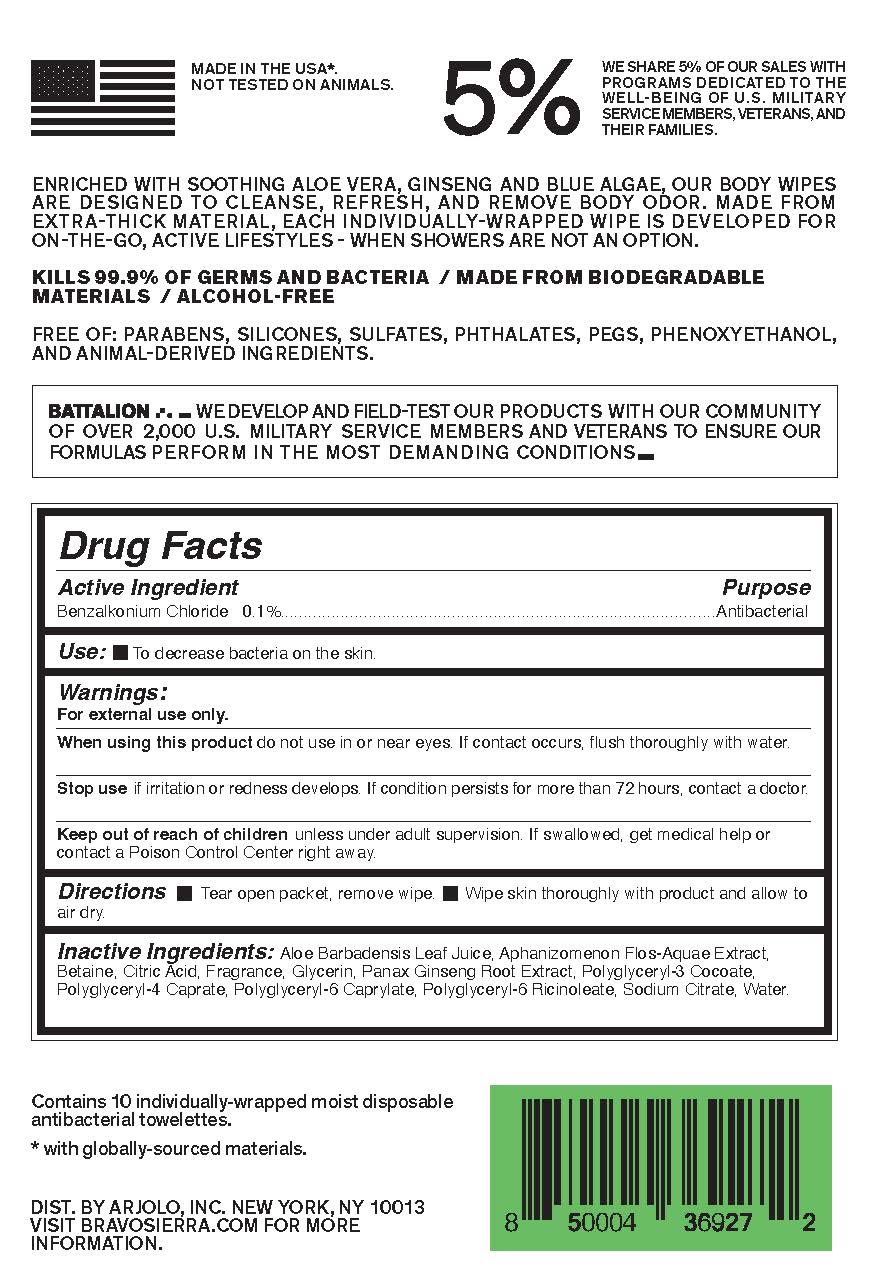 DRUG LABEL: Bravo Sierra - Antibacterial Body Wipes
NDC: 73206-100 | Form: SOLUTION
Manufacturer: Underscore USA
Category: otc | Type: HUMAN OTC DRUG LABEL
Date: 20240830

ACTIVE INGREDIENTS: BENZALKONIUM CHLORIDE 0.001 g/100 g
INACTIVE INGREDIENTS: CITRIC ACID MONOHYDRATE; ASIAN GINSENG; SODIUM CITRATE; GLYCERIN; WATER; POLYGLYCERYL-6 RICINOLEATE; POLYGLYCERYL-4 CAPRATE; APHANIZOMENON FLOSAQUAE; ALOE VERA LEAF; POLYGLYCERYL-6 CAPRYLATE; BETAINE

Bravo Sierra - Antibacterial Body Wipes

Active Ingredients

Benzalkonium Chloride 0.1%

Purpose

Antibacterial

Uses

To decrease bacteria on the skin.

Warnings

For external use only.

When using this product

do not use in or near eyes. If contact occurs, flush thoroughly with water.

Stop use

if irritation or redness develops. If condition persists for more than 72 hours, contact a doctor.

Keep out of reach of children

unless under adult supervision. If swallowed, get medical help or contact a Poison Control Center right away

Directions

Tear open packet, remove wipe.
Wipe skin thoroughly with product and allow to air dry.

Inactive Ingredients

Aloe Barbadensis Leaf Juice, Aphanizomenon Flos-Aquae Extract, Betaine, Citric Acid, Fragrance, Glycerin, Panax Ginseng Root Extract, Polyglyceryl-3 Cocoate, Polyglyceryl-4 Caprate, Polyglyceryl-6 Caprylate, Polyglyceryl-6 Ricinoleate, Sodium Citrate, Water.